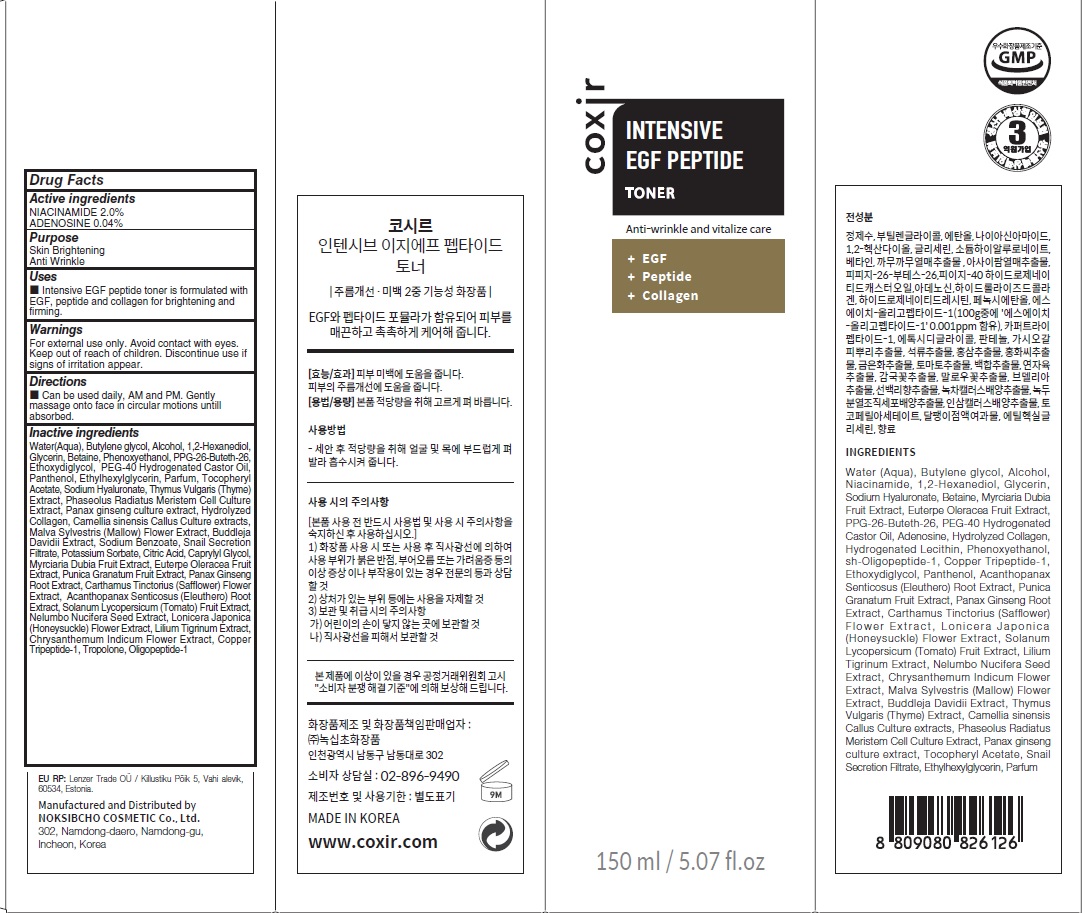 DRUG LABEL: COXIR INTENSIVE EGF PEPTIDE TONER
NDC: 73590-0074 | Form: LIQUID
Manufacturer: NOKSIBCHO cosmetic Co., Ltd.
Category: otc | Type: HUMAN OTC DRUG LABEL
Date: 20210714

ACTIVE INGREDIENTS: NIACINAMIDE 3.0 g/150 mL; ADENOSINE 0.06 g/150 mL
INACTIVE INGREDIENTS: Water; Butylene Glycol; Alcohol

Drug Facts

ACTIVE INGREDIENTS

NIACINAMIDE 2.0%
ADENOSINE 0.04%

INACTIVE INGREDIENTS

Water(Aqua), Butylene glycol, Alcohol, 1,2-Hexanediol, Glycerin, Betaine, Phenoxyethanol, PPG-26-Buteth-26, Ethoxydiglycol, PEG-40 Hydrogenated Castor Oil, Panthenol, Ethylhexylglycerin, Parfum, Tocopheryl Acetate, Sodium Hyaluronate, Thymus Vulgaris (Thyme) Extract, Phaseolus Radiatus Meristem Cell Culture Extract, Panax ginseng culture extract, Hydrolyzed Collagen, Camellia sinensis Callus Culture extracts, Malva Sylvestris (Mallow) Flower Extract, Buddleja Davidii Extract, Sodium Benzoate, Snail Secretion Filtrate, Potassium Sorbate, Citric Acid, Caprylyl Glycol, Myrciaria Dubia Fruit Extract, Euterpe Oleracea Fruit Extract, Punica Granatum Fruit Extract, Panax Ginseng Root Extract, Carthamus Tinctorius (Safflower) Flower Extract, Acanthopanax Senticosus (Eleuthero) Root Extract, Solanum Lycopersicum (Tomato) Fruit Extract, Nelumbo Nucifera Seed Extract, Lonicera Japonica (Honeysuckle) Flower Extract, Lilium Tigrinum Extract, Chrysanthemum Indicum Flower Extract, Copper Tripeptide-1, Tropolone, Oligopeptide-1

PURPOSE

Skin Brightening
Anti wrinkle

WARNINGS

For external use only.
Avoid contact with eyes.
Keep out of reach of children.
Discontinue use if signs of irritation appear.

KEEP OUT OF REACH OF CHILDREN

Uses

■ Intensive EGF peptide toner is formulated with EGF, peptide and collagen for brightening and firming.

Directions

■ Can be used daily, AM and PM aftrer cleansing. Apply evenly to face and neck. Use alone or follow with treatment routine.